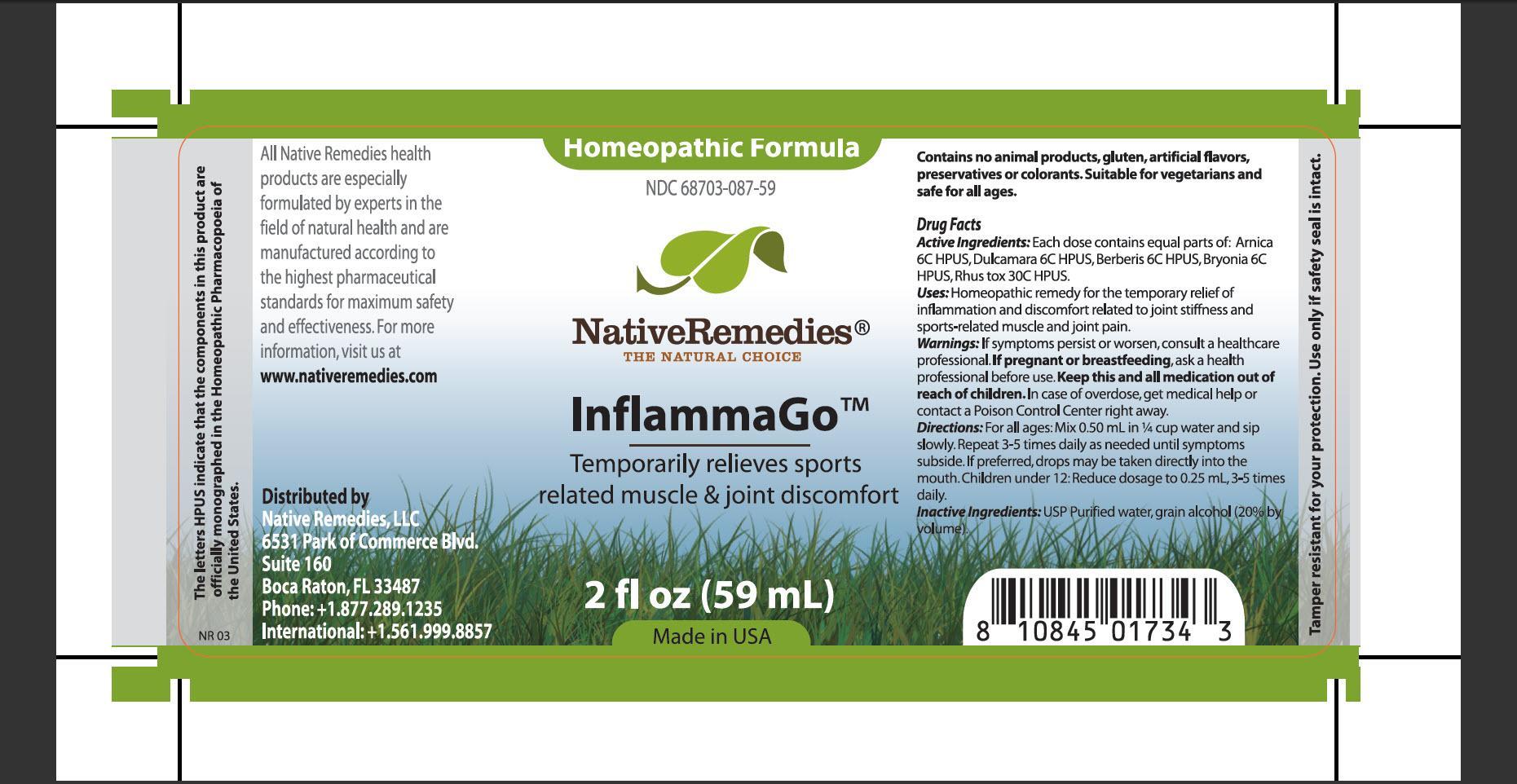 DRUG LABEL: Inflammago
NDC: 68703-087 | Form: TINCTURE
Manufacturer: Native Remedies, LLC
Category: homeopathic | Type: HUMAN OTC DRUG LABEL
Date: 20130410

ACTIVE INGREDIENTS: ARNICA MONTANA 6 [hp_C]/1 mL; SOLANUM DULCAMARA TOP 6 [hp_C]/1 mL; BERBERIS VULGARIS ROOT BARK 6 [hp_C]/1 mL; BRYONIA ALBA ROOT 6 [hp_C]/1 mL; TOXICODENDRON PUBESCENS LEAF  30 [hp_C]/1 mL
INACTIVE INGREDIENTS: WATER; ALCOHOL

InflammaGo

PURPOSE

Temporarily relieves sports related muscle and joint discomfort

ACTIVE INGREDIENT

Active Ingredients: Arnica 6C HPUS, Dulcamara 6C HPUS, Berberis 6C HPUS, Bryonia 6C HPUS, Rhus tox 30C HPUS

INDICATIONS AND USAGE

Uses: Homeopathic remedy for the temporary relief of inflammation and discomfort related to joint stiffness and sports-related muscle and joint pain

WARNINGS

Warnings: If symptoms persist or worsen, consult a healthcare professional

PREGNANCY OR BREAST FEEDING

If pregnant or breastfeeding, ask a health professional before use

KEEP OUT OF REACH OF CHILDREN

Keep this and all medication out of reach of children

OVERDOSAGE

In case of overdose, get medical help or contact a Poison Control Center right away

DOSAGE AND ADMINISTRATION

Directions: For all ages: mix 0.50 mL in 1/4 cup water and sip slowly. Repeat 3-5 times daily as needed until symptoms subside. If preferred, drops may betaken directly into the mouth. Children under 12: Reduce dosage to 0.25 mL, 3-5 times daily

INACTIVE INGREDIENT

Inactive Ingredients: USP Purified water, grain alcohol (20% by volume)

PATIENT COUNSELING INFORMATION

The letters HPUS indicate that the components in this product are officially monographed in the Homeopathic Pharmacopoeia of the United States

All Native Remedies health products are especially formulated by experts in the field of natural health and are manufactured according to the highest pharmaceutical standards for maximum safety and effectiveness. For more information, visit us at www.nativeremedies.com

Distributed by
Native Remedies, LLC
6531 Park of Commerce Blvd.
Suite 160
Boca Raton, FL 33487
Phone:+1.877.289.1235
International:+1.561.999.8857

Contains no animal products, gluten, artificial flavors, preservatives or colorants. Suitable for vegetarians and safe for all ages

STORAGE AND HANDLING

Tamper resistant for your protection. Use only if safety seal is intact